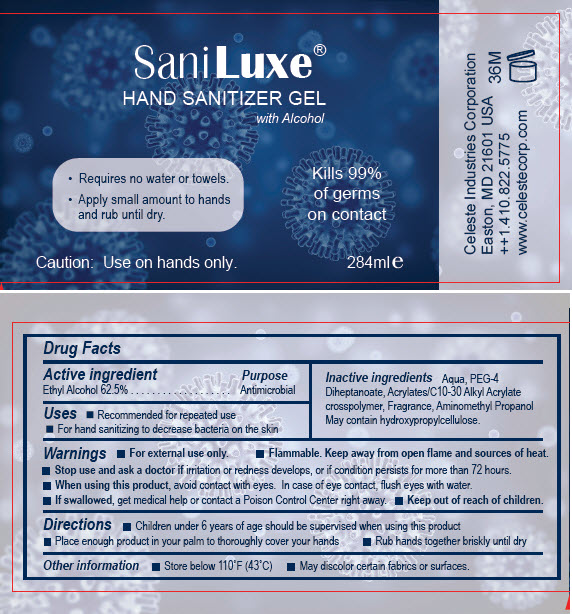 DRUG LABEL: Sani Luxe Hand Sanitizer with Alcohol
NDC: 71489-007 | Form: GEL
Manufacturer: Celeste Industries Corporation
Category: otc | Type: HUMAN OTC DRUG LABEL
Date: 20240708

ACTIVE INGREDIENTS: ALCOHOL 0.625 mL/1 mL
INACTIVE INGREDIENTS: WATER; PEG-4 DIHEPTANOATE; CARBOMER COPOLYMER TYPE A (ALLYL PENTAERYTHRITOL CROSSLINKED); AMINOMETHYLPROPANOL; HYDROXYPROPYL CELLULOSE, UNSPECIFIED

Sani Luxe® Hand Sanitizer Gel with Alcohol

Drug Facts

Active ingredient

Ethyl Alcohol 62.5%

Purpose

Antimicrobial

Uses

- Recommended for repeated use
- For hand sanitizing to decrease bacteria on the skin

Warnings

- For external use only.
- Flammable. Keep away from open flame and sources of heat.

- Stop use and ask a doctor if irritation or redness develops, or if condition persists for more than 72 hours.

- When using this product, avoid contact with eyes. In case of eye contact, flush eyes with water.
- If swallowed, get medical help or contact a Poison Control Center right away.

- Keep out of reach of children.

Directions

- Children under 6 years of age should be supervised when using this product
- Place enough product in your palm to thoroughly cover your hands
- Rub hands together briskly until dry

Other information

- Store below 110°F (43°C)
- May discolor certain fabrics or surfaces.

Inactive ingredients

Aqua, PEG-4 Diheptanoate, Acrylates/C10-30 Alkyl Acrylate crosspolymer, Fragrance, Aminomethyl Propanol

May contain hydroxypropylcellulose.

PACKAGE LABEL

Sani Luxe®
HAND SANITIZER GEL
with Alcohol

- Requires no water or towels.
- Apply small amount to hands
  and rub until dry.

Kills 99%
of germs
on contact

Caution: Use on hands only.

284ml e